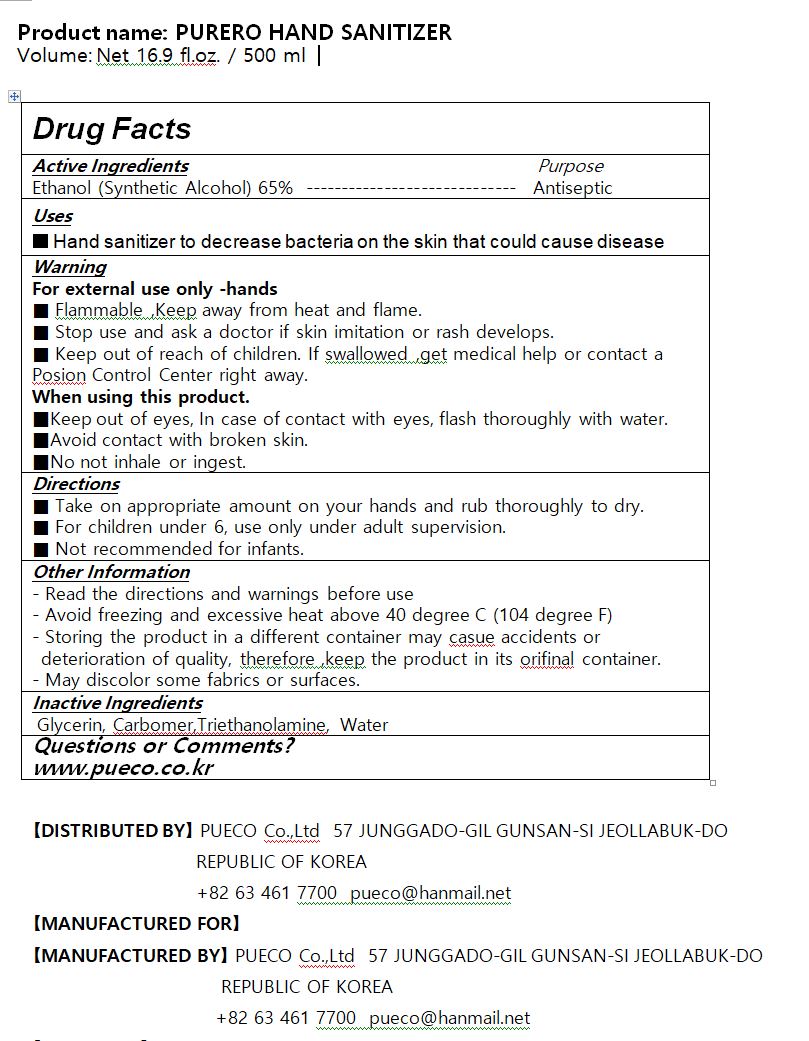 DRUG LABEL: PURERO HAND SANITIZER
NDC: 77926-0001 | Form: GEL
Manufacturer: PUECO
Category: otc | Type: HUMAN OTC DRUG LABEL
Date: 20200711

ACTIVE INGREDIENTS: ALCOHOL 65 mL/100 mL
INACTIVE INGREDIENTS: TROLAMINE; CARBOMER 940; GLYCERIN

Active Ingredient(s)

alcohol

Purpose

Hand sanitizer to decrease bacteria on the skin that could cause disease

Use

 Hand sanitizing to help reduce bacteria on the skin

Warnings

For external use only.
Flammable, keep away from fire or flame.
When using this product, avoid contact with the eyes. In case of contact, rinse eyes thoroughly with water.
Stop use and ask a doctor if irritation or redness appears and lasts.

 Keep out of reach of children. If swallowed, get medical help or contact a Poison Control Center immediately.

Directions

for external use only

INACTIVE INGREDIENT

Glycerin, Carbomer,Triethanolamine, Water